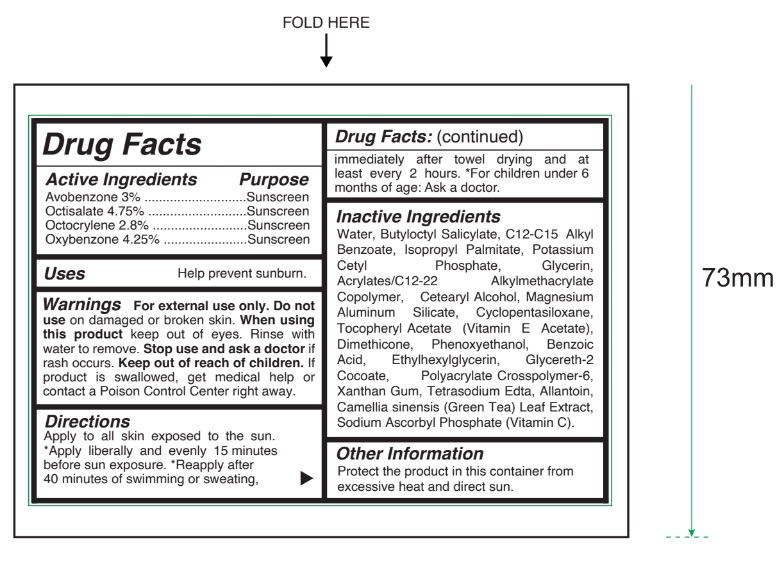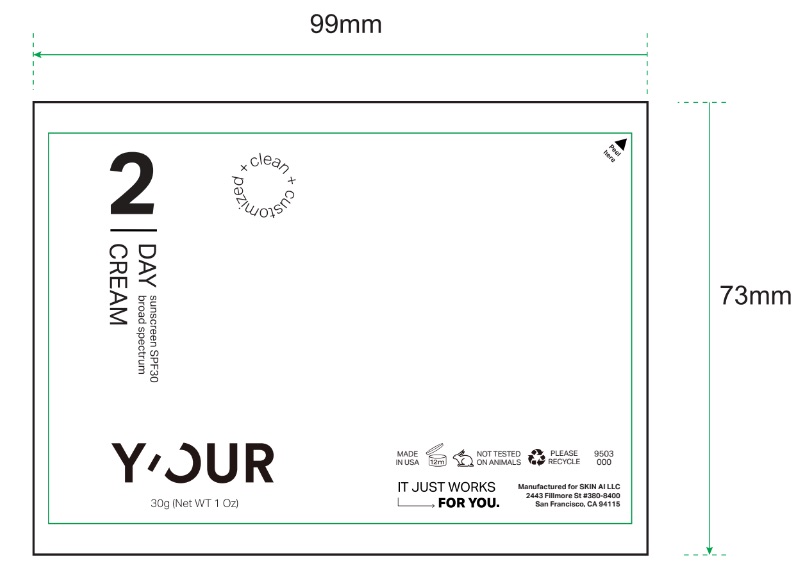 DRUG LABEL: YOUR Day Cream Sunscreen Broad Spectrum SPF 30
NDC: 84229-0017 | Form: CREAM
Manufacturer: Skin Ai, LLC
Category: otc | Type: HUMAN OTC DRUG LABEL
Date: 20240910

ACTIVE INGREDIENTS: OXYBENZONE 4.25 g/100 g; OCTOCRYLENE 2.8 g/100 g; AVOBENZONE 3 g/100 g; OCTISALATE 4.75 g/100 g
INACTIVE INGREDIENTS: BUTYL ACRYLATE/C16-C20 ALKYL METHACRYLATE/METHACRYLIC ACID/METHYL METHACRYLATE COPOLYMER; POTASSIUM CETYL PHOSPHATE; MAGNESIUM ALUMINUM SILICATE; .ALPHA.-TOCOPHEROL ACETATE, DL-; ALLANTOIN; SODIUM ASCORBYL PHOSPHATE; ISOPROPYL PALMITATE; CYCLOMETHICONE 5; CETOSTEARYL ALCOHOL; ALKYL (C12-15) BENZOATE; EDETATE SODIUM; BENZOIC ACID; GREEN TEA LEAF; GLYCERETH-2 COCOATE; BUTYLOCTYL SALICYLATE; DIMETHICONE; XANTHAN GUM; AMMONIUM ACRYLOYLDIMETHYLTAURATE, DIMETHYLACRYLAMIDE, LAURYL METHACRYLATE AND LAURETH-4 METHACRYLATE COPOLYMER, TRIMETHYLOLPROPANE TRIACRYLATE CROSSLINKED (45000 MPA.S); PHENOXYETHANOL; WATER; GLYCERIN; ETHYLHEXYLGLYCERIN

YOUR Day Cream Sunscreen Broad Spectrum SPF 30 30 g (1 oz)

Active ingredient

Avobenzone 3%

Octisalate 4.75%

Octocrylene 2.8%

Oxybenzone 4.25%

Purpose

Sunscreen

Uses

Help prevent sunburn.

Warnings

- For external use only

Do not use

on damaged or broken skin.

When using this product

keep out of eyes. Rinse with water to remove.

Stop use and ask a doctor

if rash occurs.

Keep out of reach of children.

If product is swallowed, get medical help or contact a Poison Control Center right away.

Directions

Apply to all skin exposed to the sun. *Apply liberally and evenly 15 minutes before sun exposure. *Reapply after 40 minutes of swimming or sweating, immediately after towel drying and at least every 2 hours. *For children under 6 months of age: Ask a doctor.

Inactive ingredients

Water (Aqua), Butyloctyl Salicylate, C12-15 Alkyl Benzoate, Isopropyl Palmitate, Potassium Cetyl Phosphate, Glycerin, Acrylates / C12-22 Alkyl Methacrylate Copolymer, Cetearyl Alcohol, Magnesium Aluminum Silicate, Cyclopentasiloxane, Tocopheryl Acetate (Vitamin E), Dimethicone, Phenoxyethanol, Benzoic Acid, Ethylhexylglycerin, Glycereth-2 Cocoate, Polyacrylate Crosspolymer-6, Xanthan Gum, Tetrasodium Ethylenediaminetetraacetate, Allantoin, Camellia Sinensis (Green Tea) Leaf Extract, Sodium Ascorbyl Phosphate (Vitamin C).

Other information

Protect the product in this container from excessive heat and direct sun.

Principal Display Panel

clean + customized

2

DAY

CREAM

sunscreen SPF30

broadspectrum

Y'OUR

30 g (Net WT 1 Oz)